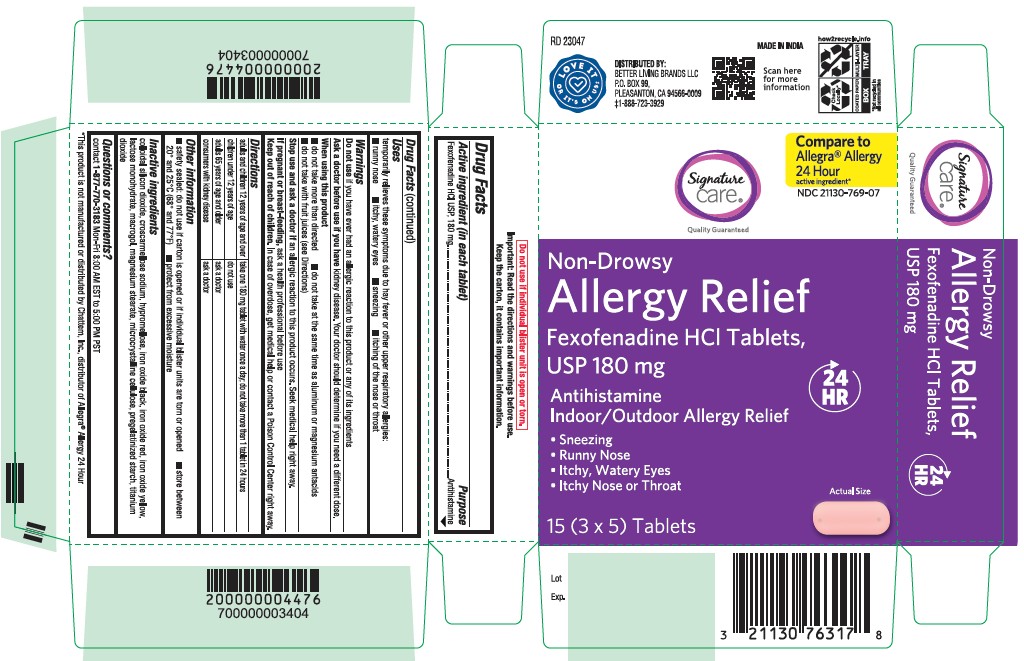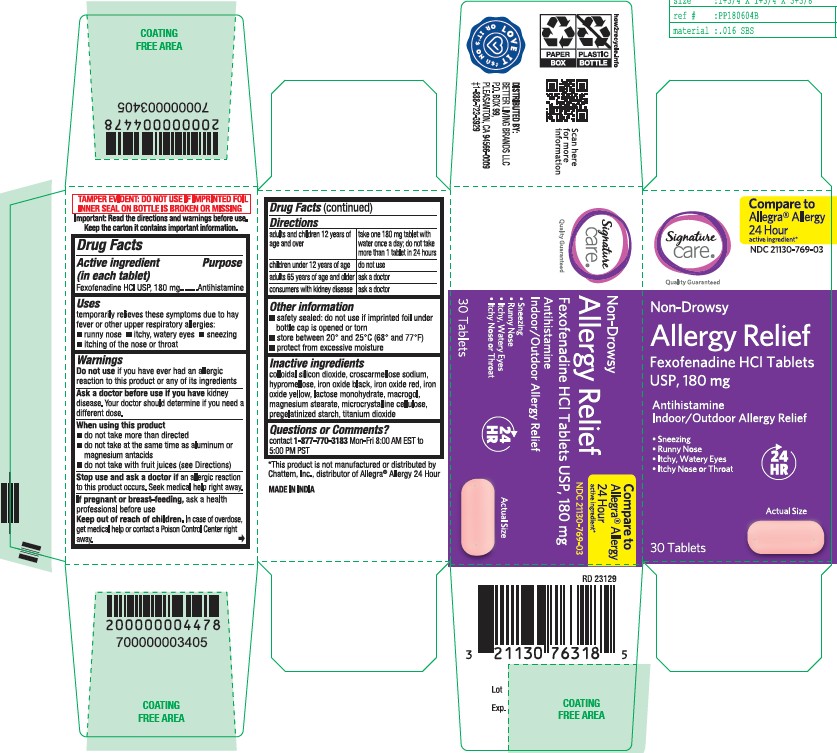 DRUG LABEL: Fexofenadine HCL
NDC: 21130-769 | Form: TABLET
Manufacturer: Safeway, Inc
Category: otc | Type: HUMAN OTC DRUG LABEL
Date: 20251219

ACTIVE INGREDIENTS: FEXOFENADINE HYDROCHLORIDE 180 mg/1 1
INACTIVE INGREDIENTS: MAGNESIUM STEARATE; MICROCRYSTALLINE CELLULOSE; FERROSOFERRIC OXIDE; FERRIC OXIDE RED; FERRIC OXIDE YELLOW; POLYETHYLENE GLYCOL 6000; SILICON DIOXIDE; TITANIUM DIOXIDE; HYPROMELLOSE 2910 (15 MPA.S); LACTOSE MONOHYDRATE; CROSCARMELLOSE SODIUM; STARCH, CORN

Fexofenadine Hydrochloride Tablets, USP 180mg
Allergy Relief
Non-Drowsy
Antihistamine
Indoor/Outdoor Allergy Relief
■ Sneezing
■ Runny Nose
■ Itchy, Watery Eyes
■ Itchy Nose or Throat

Active Ingrdient (in each tablet)

Fexofenadine HCL Tablets, USP 180mg

Purpose

Antihistamine

Uses

temporarily relieves these symptoms due to hay fever or other upper respiratory allergies:
■ runny nose ■ itchy, watery eyes ■ sneezing ■ itching of the nose or throat

Do not use

if you have ever had an allergic reaction to this product or any of its ingredients

Ask a doctor before use if you have

kidney disease. Your doctor should determine if you need a different dose.

When using this product

■ do not take more than directed ■ do not take at the same time as aluminum or magnesium antacids
■ do not take with fruit juices (see Directions)

Stop use and ask a doctor if

an allergic reaction to this product occurs. Seek medical help right away.

If pregnant or breast-feeding,

ask a health professional before use

Keep out of reach of children.

In case of overdose, get medical help or contact a Poison Control Center right away.

Directions

adults and children 12 years of age and over: take one 180 mg tablet with water once a day; do not take more than 1 tablet in 24 hours
children under 12 years of age: do not use
adults 65 years of age and older: ask a doctor
consumers with kidney disease: ask a doctor

Other information

■ safety sealed: do not use if carton is opened or if individual blister units are torn or opened ■ store between
20° and 25°C (68° and 77°F) ■ protect from excessive moisture

Inactive ingredients

colloidal silicon dioxide, croscarmellose sodium, hypromellose, iron oxide black, iron oxide red, iron oxide yellow,
lactose monohydrate, macrogol, magnesium stearate, microcrystalline cellulose, pregelatinized starch, titanium
dioxide

Questions or comments?

contact 1-877-770-3183 Mon-Fri 8:00 AM EST to 5:00 PM PST